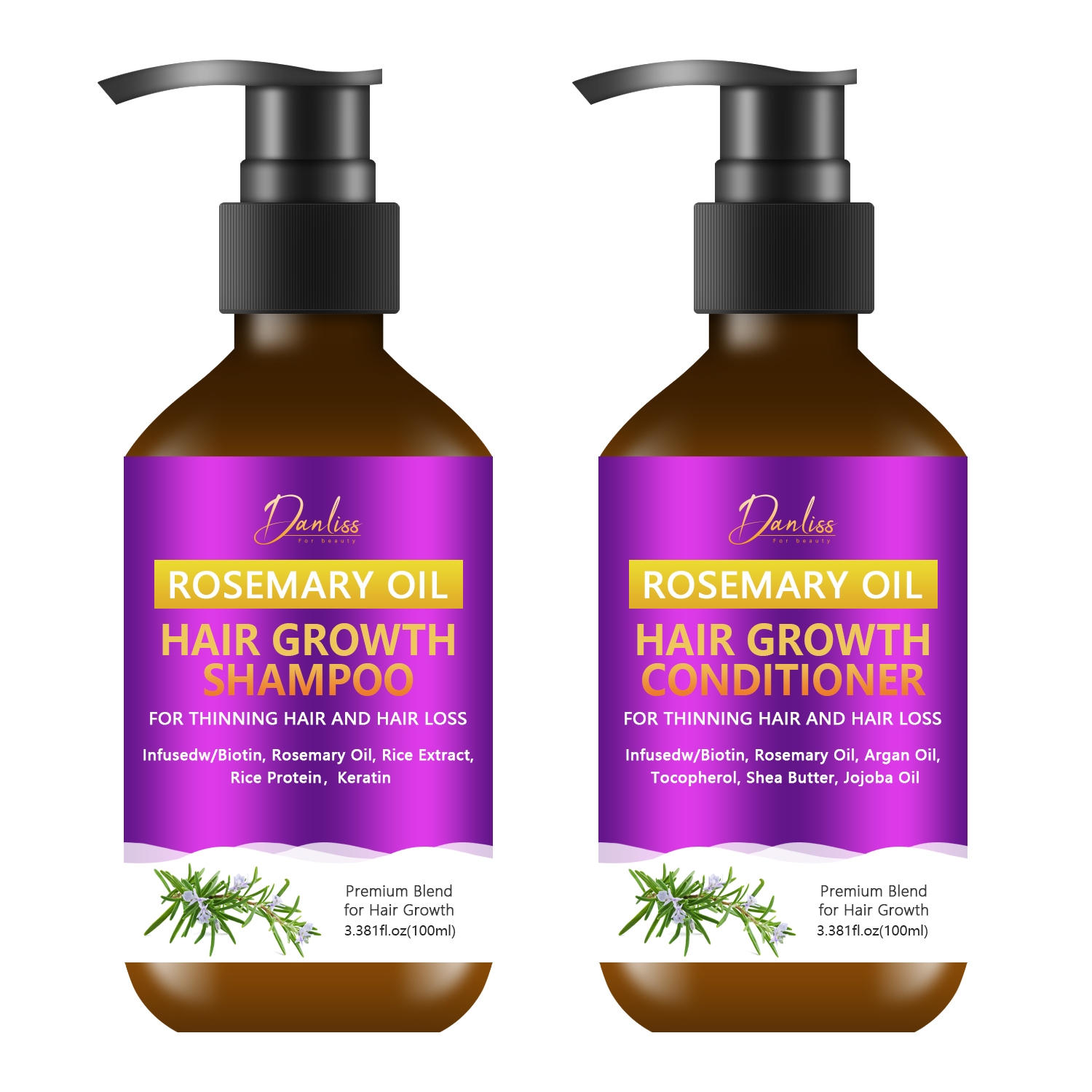 DRUG LABEL: Rosemary OilShampoo And Conditioner Set
NDC: 84025-201 | Form: SHAMPOO
Manufacturer: Guangzhou Yanxi Biotechnology Co., Ltd
Category: otc | Type: HUMAN OTC DRUG LABEL
Date: 20241008

ACTIVE INGREDIENTS: SORBITOL 5 mg/100 mL; BIOTIN 4 mg/100 mL
INACTIVE INGREDIENTS: WATER

DOSAGE AND ADMINISTRATION

Massage wet hair with shampoo,ather and rinse thoroughly.

WARNINGS

keep out of children

INACTIVE INGREDIENT

Aqua

INDICATIONS AND USAGE

For daily hair care

keep out of children

PURPOSE

For thinning hair and hair loss